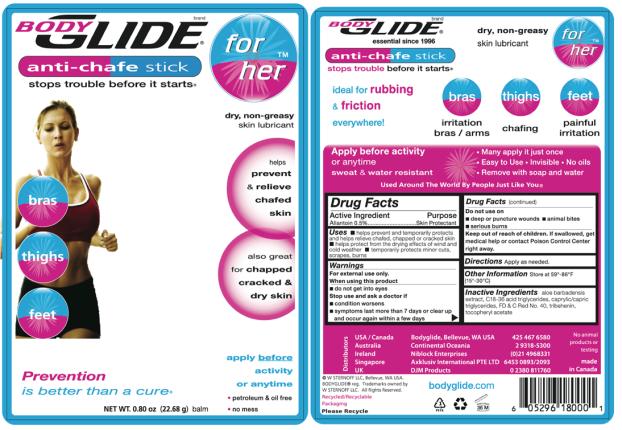 DRUG LABEL: Bodyglide For Her
NDC: 15197-009 | Form: STICK
Manufacturer: W STERNOFF LLC
Category: otc | Type: HUMAN OTC DRUG LABEL
Date: 20091212

ACTIVE INGREDIENTS: ALLANTOIN 5 mg/1 g
INACTIVE INGREDIENTS: ALOE; .ALPHA.-TOCOPHEROL ACETATE, D-; TRIBEHENIN; MEDIUM-CHAIN TRIGLYCERIDES; FD&C RED NO. 40

Bodyglide For Her

Active Ingredient:

Allantoin 0.5%

Purpose

Skin Protectant

Uses

- helps prevent and helps relieve chafed, chapped or cracked skin
- helps protect from the drying effects of wind and cold weather
- temporarily protects minor cuts, scrapes, burns

Warnings

For external use only.

When using this product

- do not get into eyes

Stop use and ask a doctor if

- condition worsens
- symptoms last more than 7 days or clear up and occur again within a few days

Do not use on

- deep or puncture wounds
- animal bites
- serious burns

Keep out of reach of children. If swallowed, get medical help or contact Poison Control Center right away.

Directions

Apply as needed.

Inactive Ingredients

aloe barbadensis extract, C18-36 acid triglycerides, caprylic/capric triglycerides, FD & C Red No. 40, tocopheryl acetate, tribehenin

Questions +1 425.467.6580

Distributor: Bodyglide, Bellevue, WA USA

Made in Canada

Principal Display Panel

BODYGLIDE®

For Her

anti-chafe stick

balm

dry, non-greasy skin lubricant

helps prevent & relieve chafed skin
also great for chapped, cracked & dry skin

bras, thighs, feet

apply before activity or anytime

petroleum & oil free

no mess

NET WT. 0.80 oz (22.68 g)